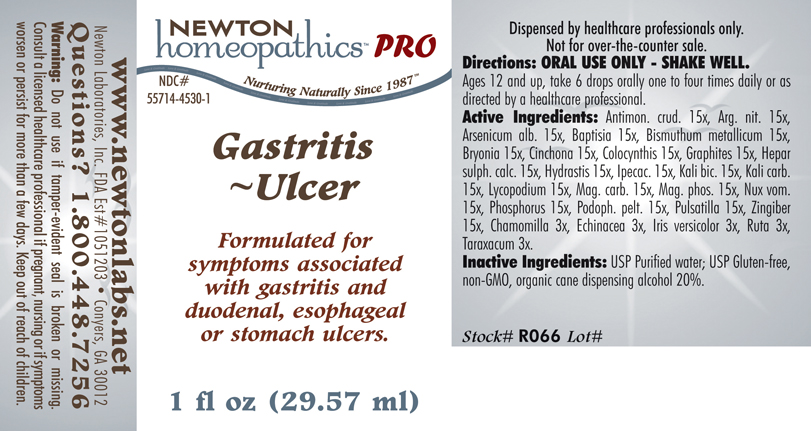 DRUG LABEL: Gastritis - Ulcer 
NDC: 55714-4530 | Form: LIQUID
Manufacturer: Newton Laboratories, Inc.
Category: homeopathic | Type: HUMAN PRESCRIPTION DRUG LABEL
Date: 20110601

ACTIVE INGREDIENTS: Antimony Trisulfide 15 [hp_X]/1 mL; Silver Nitrate 15 [hp_X]/1 mL; Arsenic Trioxide 15 [hp_X]/1 mL; Baptisia Tinctoria 15 [hp_X]/1 mL; Bismuth 15 [hp_X]/1 mL; Bryonia Alba Root 15 [hp_X]/1 mL; Cinchona Officinalis Bark 15 [hp_X]/1 mL; Citrullus Colocynthis Fruit Pulp 15 [hp_X]/1 mL; Graphite 15 [hp_X]/1 mL; Calcium Sulfide 15 [hp_X]/1 mL; Goldenseal 15 [hp_X]/1 mL; Ipecac 15 [hp_X]/1 mL; Potassium Dichromate 15 [hp_X]/1 mL; Potassium Carbonate 15 [hp_X]/1 mL; Lycopodium Clavatum Spore 15 [hp_X]/1 mL; Magnesium Carbonate 15 [hp_X]/1 mL; Magnesium Phosphate, Dibasic Trihydrate 15 [hp_X]/1 mL; Strychnos Nux-vomica Seed 15 [hp_X]/1 mL; Phosphorus 15 [hp_X]/1 mL; Podophyllum 15 [hp_X]/1 mL; Pulsatilla Vulgaris 15 [hp_X]/1 mL; Ginger 15 [hp_X]/1 mL; Matricaria Recutita 3 [hp_X]/1 mL; Echinacea, Unspecified 3 [hp_X]/1 mL; Iris Versicolor Root 3 [hp_X]/1 mL; Ruta Graveolens Flowering Top 3 [hp_X]/1 mL; Taraxacum Officinale 3 [hp_X]/1 mL
INACTIVE INGREDIENTS: Alcohol

Gastritis - Ulcer

INDICATIONS & USAGE SECTION

Gastritis - Ulcer Formulated for symptoms associated with gastritis and duodenal, esophageal or stomach ulcers.

DOSAGE & ADMINISTRATION SECTION

Directions: ORAL USE ONLY - SHAKE WELL. Ages 12 and up, take 6 drops orally one to four times daily or as directed by a healthcare professional.

ACTIVE INGREDIENT SECTION

Antimon. crud. 15x, Arg. nit. 15x, Arsenicum alb. 15x, Baptisia 15x, Bismuthum metallicum 15x, Bryonia 15x, Cinchona 15x, Colocynthis 15x, Graphites 15x, Hepar sulph. calc. 15x, Hydrastis 15x, Ipecac. 15x, Kali bic. 15x, Kali carb.15x, Lycopodium 15x, Mag. carb. 15x, Mag. phos. 15x, Nux vom.15x, Phosphorus 15x, Podoph. pelt. 15x, Pulsatilla 15x, Zingiber 15x, Chamomilla 3x, Echinacea 3x, Iris versicolor 3x, Ruta 3x, Taraxacum 3x.

PURPOSE SECTION

Formulated for symptoms associated with gastritis and duodenal, esophageal or stomach ulcers.

INACTIVE INGREDIENT SECTION

Inactive Ingredients: USP Purified Water; USP Gluten-free, non-GMO, organic cane dispensing alcohol 20%.

QUESTIONS? SECTION

www.newtonlabs.net Newton Laboratories, Inc. FDA Est # 1051203 - Conyers, GA 30012
Questions? 1.800.448.7256

WARNINGS SECTION

Warning: Do not use if tamper - evident seal is broken or missing. Consult a licensed healthcare professional if pregnant, nursing or if symptoms worsen or persist for more than a few days. Keep out of reach of children.

PREGNANCY OR BREAST FEEDING SECTION

Consult a licensed healthcare professional if pregnant, nursing or if symptoms worsen or persist for more than a few days.

KEEP OUT OF REACH OF CHILDREN SECTION

Keep out of reach of children.